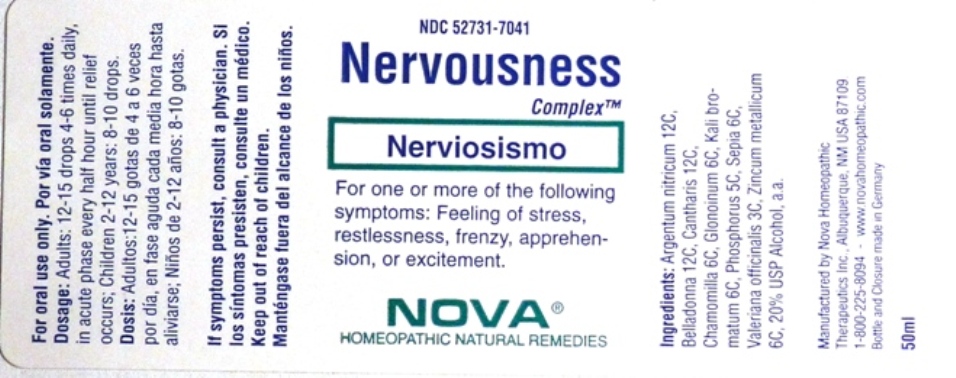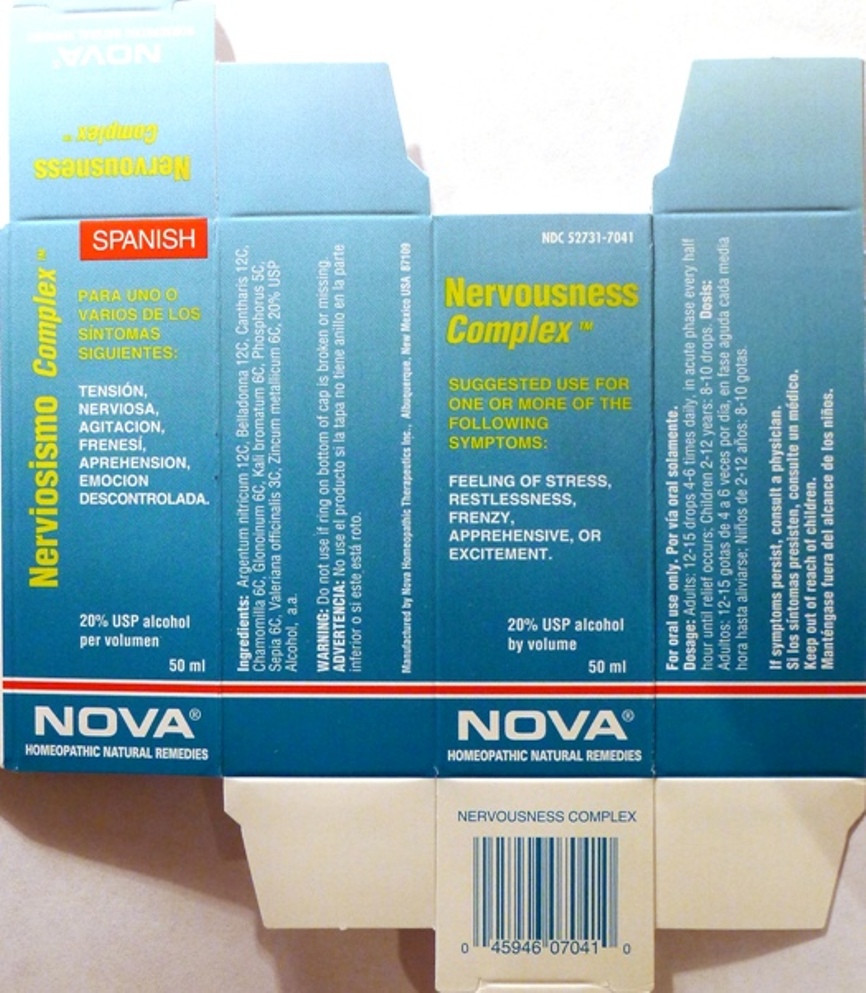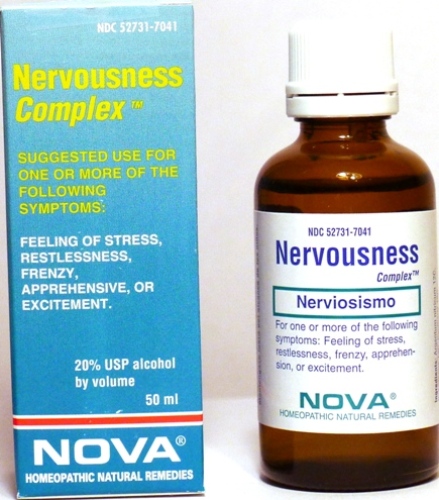 DRUG LABEL: Nervousness Complex
NDC: 52731-7041 | Form: LIQUID
Manufacturer: Nova Homeopathic Therapeutics, Inc.
Category: homeopathic | Type: HUMAN OTC DRUG LABEL
Date: 20110601

ACTIVE INGREDIENTS: SILVER NITRATE 12 [hp_C]/1 mL; ATROPA BELLADONNA 12 [hp_C]/1 mL; LYTTA VESICATORIA 12 [hp_C]/1 mL; MATRICARIA RECUTITA 6 [hp_C]/1 mL; NITROGLYCERIN 6 [hp_C]/1 mL; POTASSIUM BROMIDE 6 [hp_C]/1 mL; PHOSPHORUS 5 [hp_C]/1 mL; SEPIA OFFICINALIS JUICE 6 [hp_C]/1 mL; VALERIAN 3 [hp_C]/1 mL; ZINC 6 [hp_C]/1 mL
INACTIVE INGREDIENTS: ALCOHOL

Nervousness Complex

Purpose:

Suggested use for one or more of the following symptoms:

Feeling of stress,restlessness,frenzy, apprehensive,or excitement.

Usage and Dosage:

For oral use only.

DOSAGE AND ADMINISTRATION

Adults:
In Acute Phase:
12-15 drops, every half hour until relief occurs
When Relief Occurs:
12-15 drops, 4-6 times per day
Children 2-12 years:
8-10 drops, 4-6 times per day

Warnings:

Keep out of reach of children.

WARNINGS

If symptoms persist, consult a physician.
Do not use if ring on bottom of cap is broken or missing.

Active Ingredients:

Argentum nitricum 12C, Belladonna 12C, Cantharis 12C, Chamomilla 6C, Glonoinum 6C, Kali bromatum 6C, Phosphorus 5C, Sepia 6C, Valeriana officinalis 3C, Zincum metallicum 6C

Inactive Ingredients:

Alcohol, 20% USP

QUESTIONS

Manufactured by Nova Homeopathic Therapeutics Inc., Albuquerque, New Mexico USA 87109
1-800-225-8094

PACKAGE LABEL

Nervousness Complex Product

Nervousness Complex Bottle Label

Nervousness Complex Box